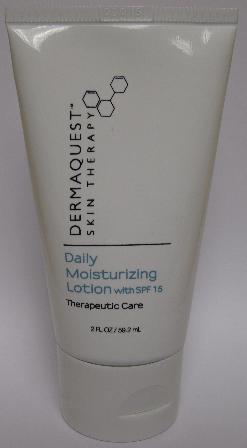 DRUG LABEL: Dermaquest Skin Therapy Daily Moisturizing SPF 15
NDC: 62742-4053 | Form: LOTION
Manufacturer: Allure Labs, Inc.
Category: otc | Type: HUMAN OTC DRUG LABEL
Date: 20100826

ACTIVE INGREDIENTS: ZINC OXIDE 95 mg/1 mL

Drug Facts

INDICATIONS AND USAGE

Optimal for daily use, this state-of-the-art lotion contains Zinc Oxide to help protect against the damaging effects of UVA and UVB rays. Cosmetically elegant and hydrating, this lotion id ideal for sensitive skin and post professional treatments.

DIRECTIONS:

Apply daily to the fingertips and gently massage into the skin. Reapply as needed. Discontinue use if irritation develops.

ACTIVE INGREDIENT:

Zinc Oxide 9.5%

INACTIVE INGREDIENTS:

Water (Aqua), Cyclomethicone, Glycerin, Glyceryl Stearate (and) PEG-100 Stearate, Sorbitol, Imperata Cyclidrica (Root) Extract, Caprylyl Glycol, Sorbitan Stearate, Lecithin, Arabidopsis Extract, Plakton Extract, Xanthan Gum, Carbomer, Ascorbyl Palmitate (Vitamin C), Tocopheryl Acetate (Vitamin E), Citric Acid, Disodium EDTA.

PACKAGE LABEL

DISTRIBUTOR:

DeramQuest Inc.

Hayward, CA 94544

dermaquestinc.com

IMAGE OF DAILY MOISTURIZING LOTION WITH SPF 15, 2 FL OZ TUBE: